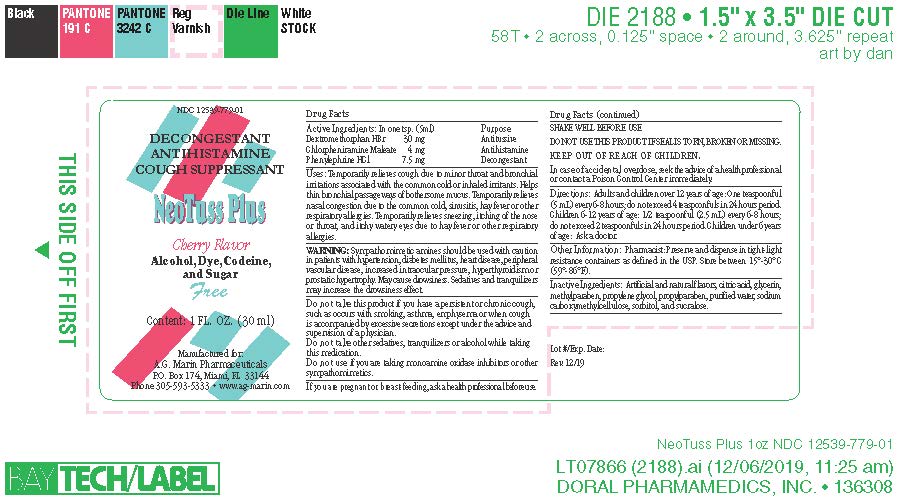 DRUG LABEL: NeoTuss Plus
NDC: 12539-779 | Form: LIQUID
Manufacturer: DORAL PHARMAMEDICS INC dba A.G. Marin Pharmaceuticals
Category: otc | Type: HUMAN OTC DRUG LABEL
Date: 20251218

ACTIVE INGREDIENTS: CHLORPHENIRAMINE MALEATE 4 mg/5 mL; DEXTROMETHORPHAN HYDROBROMIDE 30 mg/5 mL; PHENYLEPHRINE HYDROCHLORIDE 7.5 mg/5 mL
INACTIVE INGREDIENTS: PROPYLENE GLYCOL 300 mg/5 mL; SORBITOL 1750 mg/5 mL; GLYCERIN 500 mg/5 mL; CITRIC ACID 10 mg/5 mL; METHYLPARABEN 9 mg/5 mL; PROPYLPARABEN 1 mg/5 mL; SODIUM CARBOXYMETHYL STARCH 30 mg/5 mL; SUCRALOSE 7.5 mg/5 mL; WATER 2331 mg/5 mL

NeoTuss Plus Cherry Flavor

ACTIVE INGREDIENT

Dextromethorphan HBr 30 mg / 5 mL

Chlorpheniramine Maleate 4 mg / 5 mL

Phenylephrine HCl 7.5 mg / 5 mL

INACTIVE INGREDIENT

Artificial and natural flavors, citric acid, glycerin, methylparaben, propylene glycol, propylparaben, purified water, sodium carboxymethylcellulose, sorbitol, and sucralose.

PURPOSE

Antitussive, Antihistamine, and Decongestant.

Temporarily relieves cough due to minor throat and bronchial irritations associated with the common cold or inhaled irritants. Helps thin bronchial passageways of bothersome mucus.

Temporarily relieves nasal congestion due to the common cold, sinusitis, hay fever or other respiratory allergies.

Temporarily relieves sneezing, itching of the nose or throat, and itchy watery eyes due to hay fever or other respiratory allergies.

DOSAGE AND ADMINISTRATION

Adults and children over 12 years of age: One teaspoonful (5 mL) every 6-8 hours; do not exceed 4 teaspoonfuls in 24 hours period.

Children 6-12 years of age: 1/2 teaspoonful (2.5 mL) every 6-8 hours; do not exceed 2 teaspoonfuls in 24 hours period. Children under 6 years of age: Ask a doctor.

KEEP OUT OF REACH OF CHILDREN

In case of accidental overdose seek the advice of a health professional or contact a Poison Control Center immediately.

WHEN USING

Shake well before use.

Temporarily relieves cough due to minor throat and bronchial irritations associated with the common cold or inhaled irritants. Helps thin bronchial passageways of bothersome mucus.

Temporarily relieves nasal congestion due to the common cold, sinusitis, hay fever or other respiratory allergies.

Temporarily relieves sneezing, itching of the nose or throat, and itchy watery eyes due to hay fever or other respiratory allergies.

Do not use this product if the seal is torn, broken or missing.

Do not take this product if you have a persistent or chronic cough, such as occurs with smoking, asthma, emphysema or when cough is accompanied by excessive secretions except under the advice and supervision of a physician.

Do not take other sedatives, tranquilizers or alcohol while taking this medication.

Do not use if you are taking monoamine oxidase inhibitors or other sympathomimetics.

If you are pregnant or breast-feeding, ask a health professional before using this product.

WARNINGS AND PRECAUTIONS

Sympathomimetic amines should be used with caution in patients with hypertension, diabetes mellitus, heart disease, peripheral vascular disease, increased intraocular pressure, hyperthyroidism or prostatic hypertrophy. May cause drowsiness. Sedatives and tranquilizers may increase the drowsiness effect.

OTHER SAFETY INFORMATION

Pharmacist: Preserve and dispense in tight-light resistance containers as defined in the USP.

Store between 15°-30°C (59°-86°F).

Do not accept this product if the safety seal is broken or missing.

Keep a box for information.

WARNINGS

Sympathomimetic amines should be used with caution in patients with hypertension, diabetes mellitus, heart disease, peripheral vascular disease, increased intraocular pressure, hyperthyroidism or prostatic hypertrophy. May cause drowsiness. Sedatives and tranquilizers may increase the drowsiness effect.

INDICATIONS AND USAGE

Adults and children over 12 years of age: One teaspoonful (5 mL) every 6-8 hours; do not exceed 4 teaspoonfuls in 24 hours period.

Children 6-12 years of age: 1/2 teaspoonful (2.5 mL) every 6-8 hours; do not exceed 2 teaspoonfuls in 24 hours period. Children under 6 years of age: Ask a doctor.

Temporarily relieves cough due to minor throat and bronchial irritations associated with the common cold or inhaled irritants. Helps thin bronchial passageways of bothersome mucus.

Temporarily relieves nasal congestion due to the common cold, sinusitis, hay fever or other respiratory allergies.

Temporarily relieves sneezing, itching of the nose or throat, and itchy watery eyes due to hay fever or other respiratory allergies.

Package Label - Principal Display Panel

1 FL. OZ (30 mL) NDC: 12539-779-01